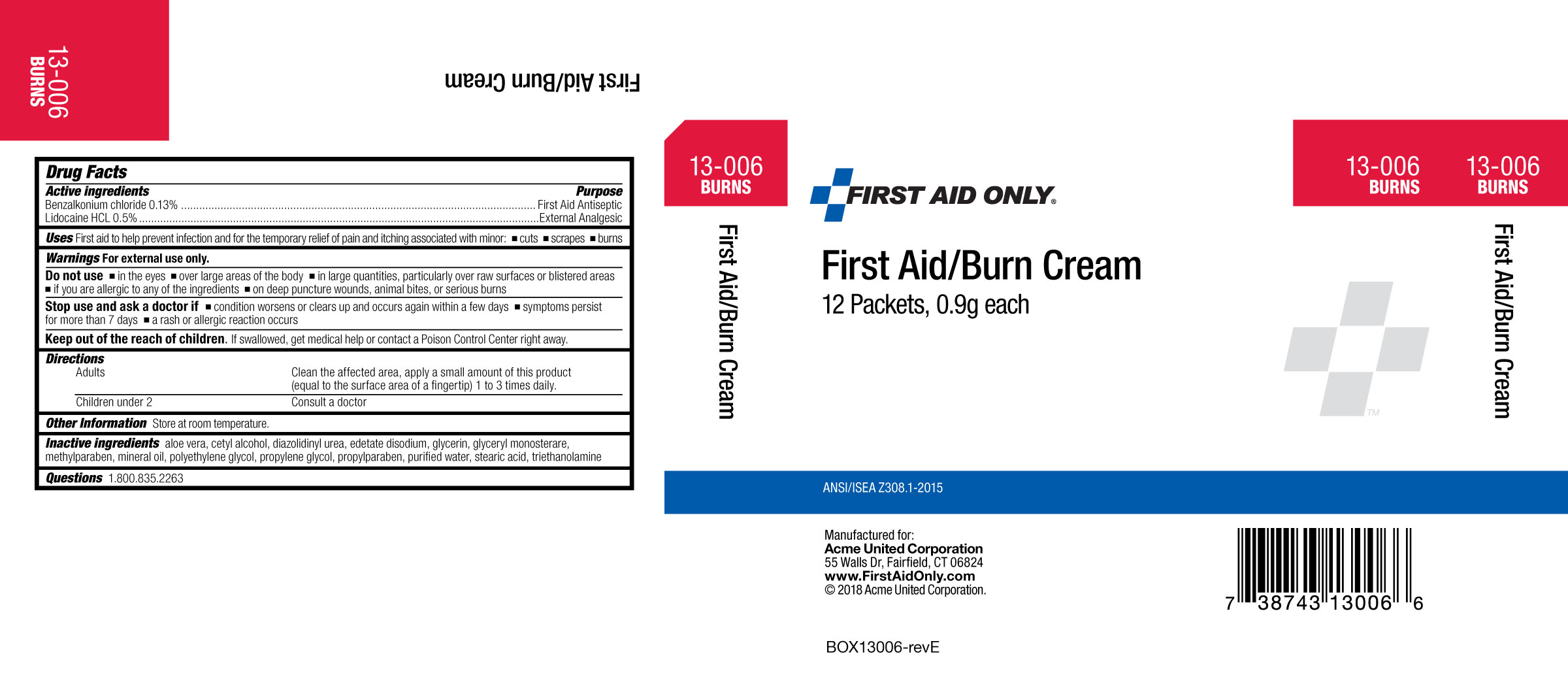 DRUG LABEL: First Aid Only First Aid/ Burn
NDC: 0924-5711 | Form: CREAM
Manufacturer: Acme United Corporation
Category: otc | Type: HUMAN OTC DRUG LABEL
Date: 20201222

ACTIVE INGREDIENTS: LIDOCAINE HYDROCHLORIDE 0.5 g/100 g; BENZALKONIUM CHLORIDE 0.13 g/100 g
INACTIVE INGREDIENTS: ALOE VERA LEAF; WATER; PROPYLPARABEN; GLYCERYL MONOSTEARATE; EDETATE DISODIUM; LIGHT MINERAL OIL; STEARIC ACID; PEG-100 STEARATE; CETYL ALCOHOL; TROLAMINE; GLYCERIN; METHYLPARABEN; PROPYLENE GLYCOL; DIAZOLIDINYL UREA

First Aid Only First Aid/Burn Cream

Active ingredients

Benzalkonium chloride 0.13%

Lidocaine HCl 0.5%

Purpose

First Aid antiseptic

External analgesic

Uses

First aid to help prevent infection and for the temporary relief of pain and itching associated with

- minor cuts

- scrapes

- burns

Warnings

For external use only.

Do not use

▪in the eyes ▪over large areas of the body ▪in large quantities, particularly over raw surfaces or blistered areas ▪if you are allergic to any of the ingredients ▪on deep puncture wounds, animal bites, or serious burns

Ask a doctor before use if you have

deep or puncture wounds, animal bites, or serious burns

When using this product

avoid contact with eyes

Stop use and ask a doctor if

▪condition worsens or clears up and occurs again within a few days

▪symptoms persist for more than 7 days

▪a rash or allergic reaction occurs

Keep out of the reach of children.

If swallowed, get medical help or contact a Poison Control Center right away.

Other information

Store at room temperature

Directions

Adults - Clean the affected area, apply a small amount of product (equal to the surface area of a fingertip) 1 to 3 times daily.

Children under 2- Consult a doctor

Inactive ingredients

aloe vera, cetyl alcohol, diazolidinyl urea, edetate disodium, glycerin, glyceryl monostearate, methylparaben, mineral oil, polyethylene glycol, propylene glycol, propylparaben, purified water, stearic acid, triethanolamine

Questions?

1-800-835-2263

PACKAGE LABEL

Carton Image